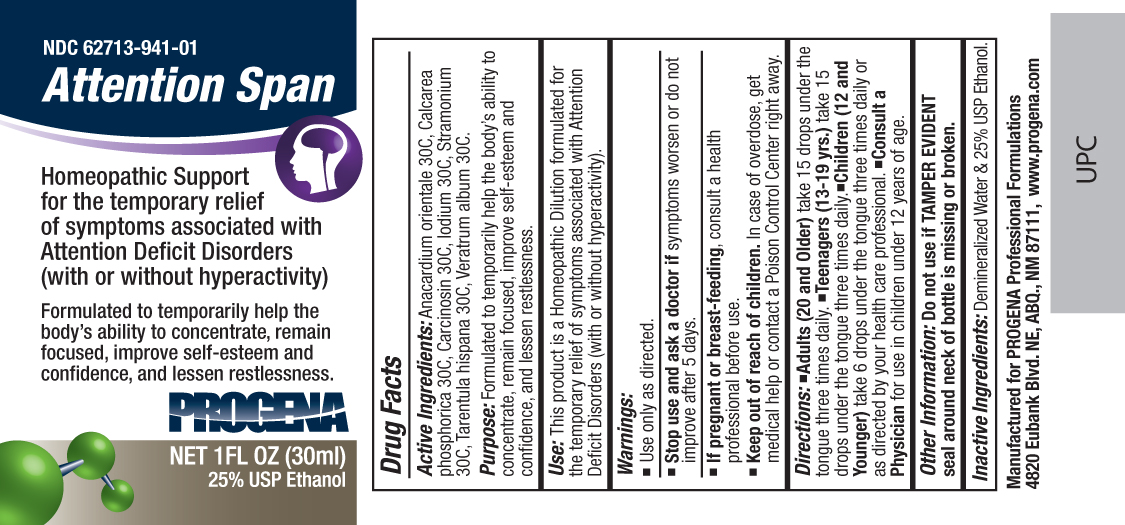 DRUG LABEL: Progena
NDC: 62713-941 | Form: LIQUID
Manufacturer: Meditrend, Inc. DBA Progena Professional Formulations
Category: homeopathic | Type: HUMAN OTC DRUG LABEL
Date: 20121205

ACTIVE INGREDIENTS: SEMECARPUS ANACARDIUM JUICE 30 [hp_C]/1 mL; TRIBASIC CALCIUM PHOSPHATE 30 [hp_C]/1 mL; HUMAN BREAST TUMOR CELL 30 [hp_C]/1 mL; IODINE 30 [hp_C]/1 mL; DATURA STRAMONIUM 30 [hp_C]/1 mL; LYCOSA TARANTULA 30 [hp_C]/1 mL; VERATRUM ALBUM ROOT 30 [hp_C]/1 mL
INACTIVE INGREDIENTS: WATER; ALCOHOL

Attention Span

ACTIVE INGREDIENT

Active Ingredients: Anacardium orientale 30C, Calcarea phosphorica 30C, Carcinosin 30C, Iodium 30C, Stramonium 30C, Tarentula hispana 30C, Veratrum album 30C.

PURPOSE

Purpose: Formulated to temporarily help the body's ability to concentrate, remain focused, improve self-esteem and confidence, and lessen restlessness.

INDICATIONS AND USAGE

Use: This product is a Homeopathic Dilution formulated for the temporary relief of symptoms associated with Attention Deficit Disorders (with or without hyperactivity).

Keep Out of Reach of Children. In case of overdose, get medical help or contact a
Poison Control Center right away.

Warnings:

- Use Only as directed.
- Stop use and ask a doctor ifsymptoms worsen or do not improve after 5 days.
- If pregnant or breast-feeding, consult a health professional before use.

DOSAGE AND ADMINISTRATION

Directions:•Adults (20 and Older) take 15 drops under the tongue three times daily.•Teenagers (13-19 yrs.) take 15 drops under the tongue three times daily.•Children (12 and Younger) take 6 drops under the tongue three times daily or as directed by your health care professional.•Consult a Physicianfor use in children under 12 years of age.

Other Information: Do not use if TAMPER EVIDENT seal around neck of bottle is missing or broken.

Inactive Ingredients: Demineralized water and 25% USP Ethanol.

PACKAGE LABEL

Manufactured for Progena Professional Formulations
4820 Eubank Blvd. NE, ABQ, NM 87111, www.progena.com